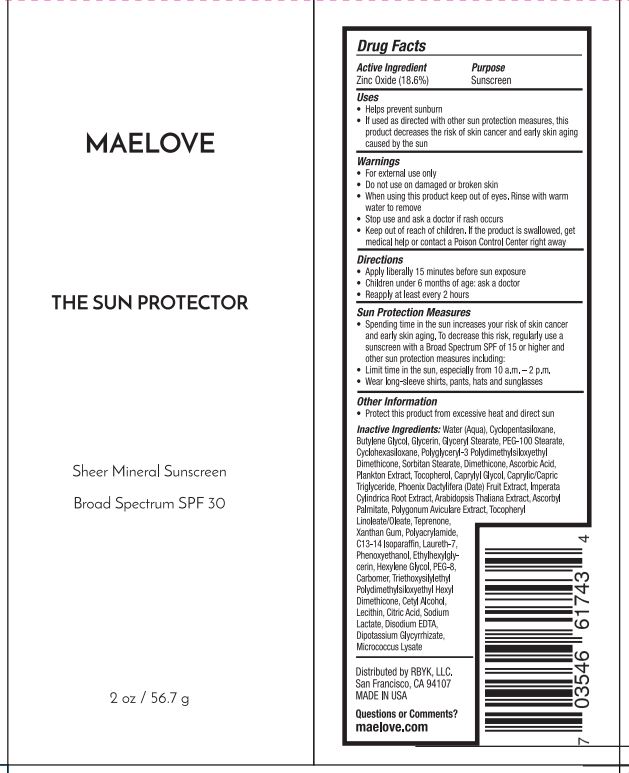 DRUG LABEL: Sheer Mineral Sunscreen Broad Spectrum SPF 30
NDC: 62742-4242 | Form: CREAM
Manufacturer: Allure Labs
Category: otc | Type: HUMAN OTC DRUG LABEL
Date: 20231213

ACTIVE INGREDIENTS: ZINC OXIDE 18.6 g/100 g
INACTIVE INGREDIENTS: WATER; POLYGLYCERYL-3 POLYDIMETHYLSILOXYETHYL DIMETHICONE (4000 MPA.S); TRIETHOXYSILYLETHYL POLYDIMETHYLSILOXYETHYL HEXYL DIMETHICONE; LECITHIN, SOYBEAN; ARABIDOPSIS THALIANA; BUTYLENE GLYCOL; SORBITAN MONOSTEARATE; DIMETHICONE; MEDIUM-CHAIN TRIGLYCERIDES; ASCORBYL PALMITATE; CYCLOMETHICONE 6; DATE; POLYGONUM AVICULARE TOP; TEPRENONE; POLYACRYLAMIDE (CROSSLINKED; 2 MOLE PERCENT BISACRYLAMIDE); CARBOMER HOMOPOLYMER, UNSPECIFIED TYPE; POLYETHYLENE GLYCOL 400; CETYL ALCOHOL; PEG-100 STEARATE; TOCOPHEROL; .ALPHA.-TOCOPHEROL ACETATE, DL-; IMPERATA CYLINDRICA ROOT; LAURETH-7; CITRIC ACID MONOHYDRATE; SODIUM LACTATE, L-; CAPRYLYL GLYCOL; CYCLOMETHICONE 5; GLYCERYL MONOSTEARATE; LINOLEIC ACID; ETHYLHEXYLGLYCERIN; EDETATE DISODIUM ANHYDROUS; GLYCYRRHIZINATE DIPOTASSIUM; MICROCOCCUS LUTEUS; C13-14 ISOPARAFFIN; PHENOXYETHANOL; HEXYLENE GLYCOL; XANTHAN GUM; GLYCERIN; ASCORBIC ACID

Drug Facts

Active Ingredients:

Zinc Oxide 18.6%

Purpose: Sunscreen

INDICATIONS AND USAGE

Uses • helps to prevent sunburn

• if used as directed with other sun protection measures (see Directions), decreases the risk of skin cancer and early skin aging caused by the sun.

Warnings For external use only

Do not use • on damaged or broken skin.

When using this product • keep out of eyes. Rinse with warm water to remove.

Stop use and ask a doctor if rash occurs.

Keep out of reach of children. If product is swallowed, get medical help, or contact a Poison Control Center right away.

DOSAGE AND ADMINISTRATION

Directions • Apply liberally 15 minutes before sun exposure.

• Children under 6 months: Ask a doctor

• Reapply: at least every 2 hours

Sun Protection Measures

• Spending time in the sun increases your risk of skin cancer and early skin aging. To decrease this risk, regularly use a sunscreen with a broad-spectrum SPF of 15 or higher and other sun protection measures including: • limit time in the sun, especially from 10 a.m. – 2 p.m. • wear long-sleeve shirts, pants, hats, and sunglasses.

Other information • Protect this product from excessive heat or direct sun.

Inactive Ingredients:

Water (Aqua),Cyclopentasiloxane, Butylene Glycol, Glycerin, Glyceryl Stearate, PEG-100 Stearate, Cyclohexasiloxane, Polyglyceryl-3 Polydimethylsiloxyethyl Dimethicone, Sorbitan Stearate, Dimethicone,Ascorbic Acid, Plankton Extract, Tocopherol, caprylyl Glycol, Caprylic/Capric Triglyceride, Phoenix Dactylifera (Date) Fruit Extract, Imperata Cylindrica Root Extract, Arabidopsis Thaliana Extract, Ascorbyl Palmitate, Polygonum Aviculare Extract,Tocopheryl Linoleate/Oleate, Teprenone, Xanthan Gum,Polyacrylamide, C13-14 Isoparaffin, Laureth-7, Phenoxyethanol, Ethylhexylglycerin, Hexylene Glycol, PEG-8, Carbomer, Triethoxysilylethyl Polydimethylsiloxyethyl Hexyl Dimethicone, Cetyl Alcohol, Lecithin, Citric Acid, Sodium Lactate, Disodium EDTA, Dipotassium Glycyrrhizate, Micrococcus Lysate.